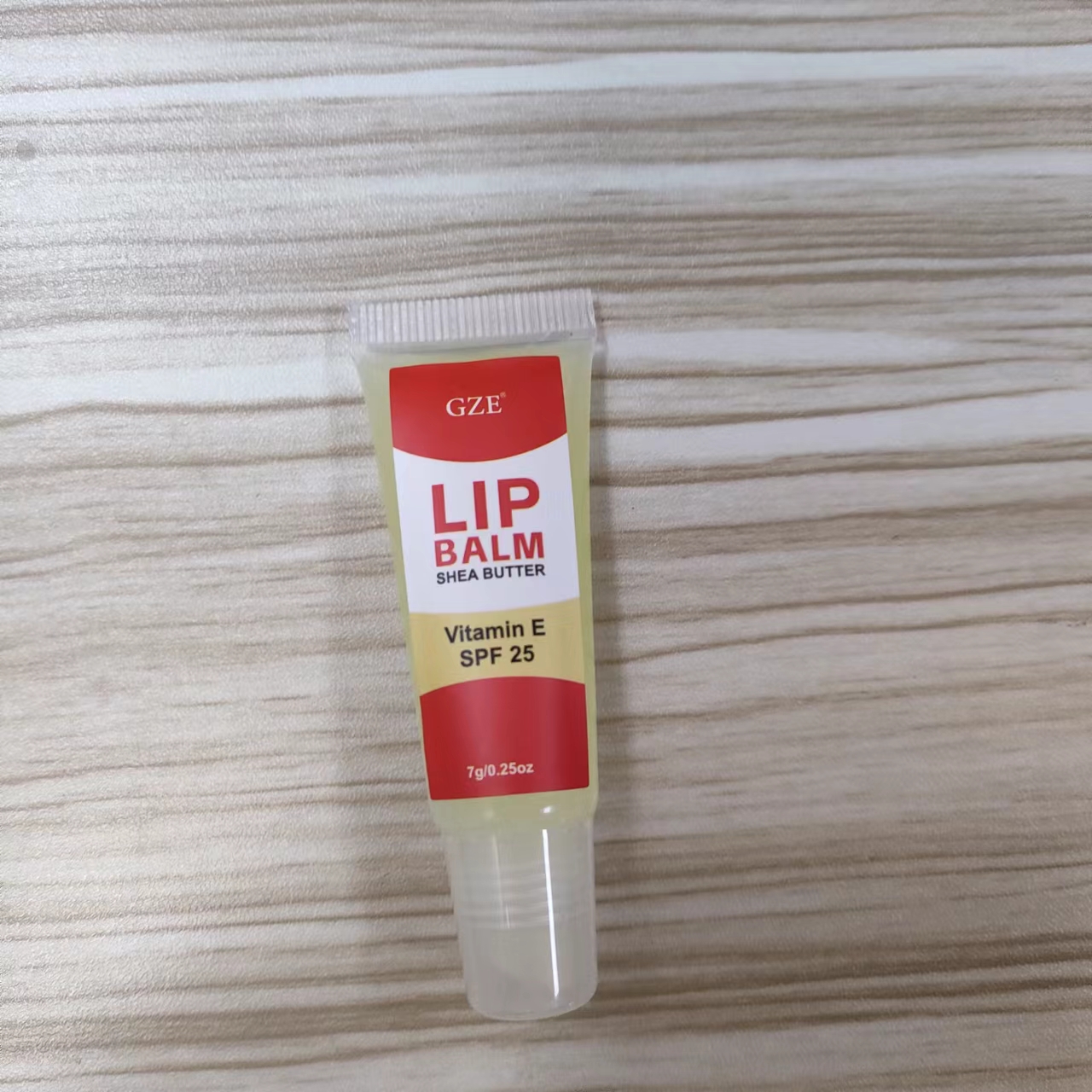 DRUG LABEL: GZE LIP BALM
NDC: 74458-282 | Form: PASTE
Manufacturer: Guangzhou Yilong Cosmetics Co., Ltd
Category: otc | Type: HUMAN OTC DRUG LABEL
Date: 20241029

ACTIVE INGREDIENTS: TOCOPHEROL 5 g/100 g
INACTIVE INGREDIENTS: BUTYROSPERMUM PARKII (SHEA) BUTTER; HELIANTHUS ANNUUS (SUNFLOWER) SEED OIL; SIMMONDSIA CHINENSIS (JOJOBA) SEED OIL

GZE LIP BALM

ACTIVE INGREDIENT

Tocopherol.

INACTIVE INGREDIENT

Helianthus Annuus (Sunflower) Seed Oil, Cera Alba, Simmondsia Chinensis (Jojoba) Seed Oil, Butyrospermum Parkii (Shea) Butter.

INDICATIONS AND USAGE

Apply generously and evenly to lips 30 minutes before going out in the sun, or whenever they feel dry or chapped.

PURPOSE

Lip care

WARNINGS

For external use only.

Stop use and ask a doctor if rash occurs.

Do not use on damaged or broken skin.

When using this product keep out of eyes. Rinse with water to remove.

Keep out of reach of children. If swallowed, get medical help or contact a Poison Control Center right away.

DOSAGE AND ADMINISTRATION

Apply generously and evenly to lips 30 minutes before going out in the sun, or whenever they feel dry or chapped.